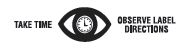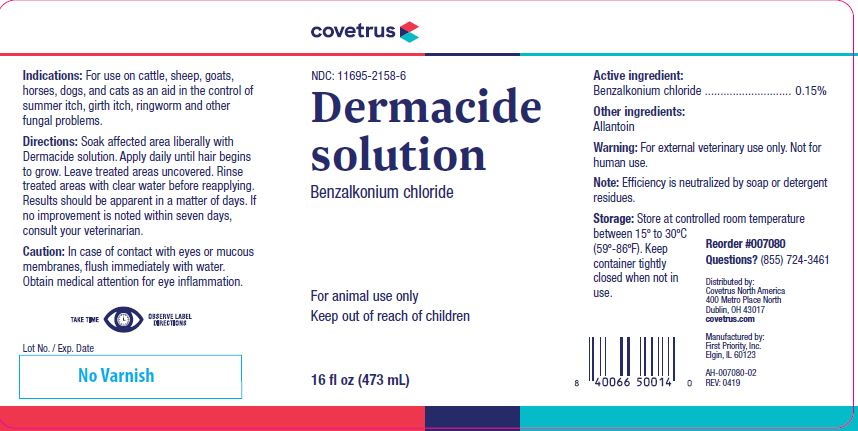 DRUG LABEL: Dermacide
NDC: 11695-2158 | Form: SOLUTION
Manufacturer: Butler Animal health Supply, LLC dba Covetrus North America
Category: animal | Type: OTC ANIMAL DRUG LABEL
Date: 20221105

ACTIVE INGREDIENTS: BENZALKONIUM CHLORIDE 3.09 mg/1 mL

Dermacide solution

STATEMENT OF IDENTITY

Benzalkonium chloride

WARNINGS AND PRECAUTIONS

For animal use only
Keep out of reach of children

HOW SUPPLIED

16 fl oz (473 mL)

Indications:

For use on cattle, sheep, goats, horses, dogs, and cats as an aid in the control of summer itch, girth itch, ringworm and other fungal problems.

Directions:

Soak affected area liberally with Dermacide solution. Apply daily until hair begins to grow. Leave treated areas uncovered. Rinse treated areas with clear water before reapplying. Results should be apparent in a matter of days. If no improvement is noted within seven days, consult your veterinarian.

Caution:

In case of contact with eyes or mucous membranes, flush immediately with water. Obtain medical attention for eye inflammation.

Active ingredient:

Benzalkonium chloride ............................ 0.15%

Other ingredients:

Allantoin

Warning:

For external veterinary use only. Not for human use.

Note:

Efficiency is neutralized by soap or detergent residues.

Storage:

Store at controlled room temperature between 15º to 30ºC (59º-86ºF). Keep container tightly closed when not in use.

INFORMATION FOR OWNERS/CAREGIVERS

Reorder #007080
Questions? (855) 724-3461
Distributed by:
Covetrus North America
400 Metro Place North
Dublin, OH 43017
covetrus.com

Manufactured by:
First Priority, Inc.
Elgin, IL 60123